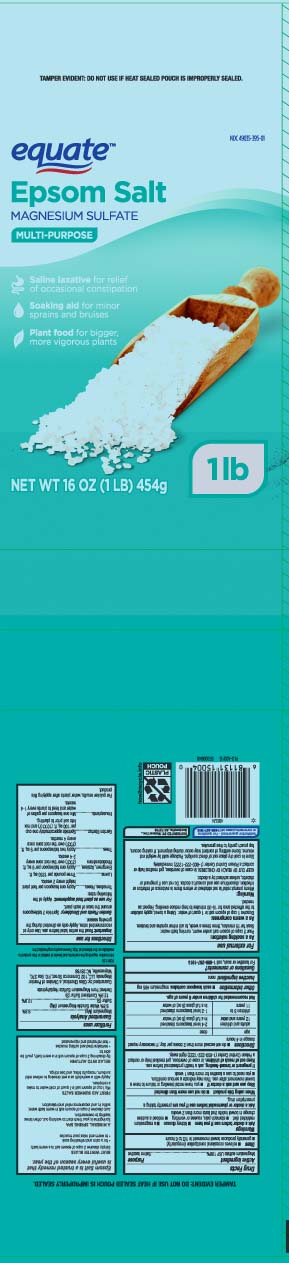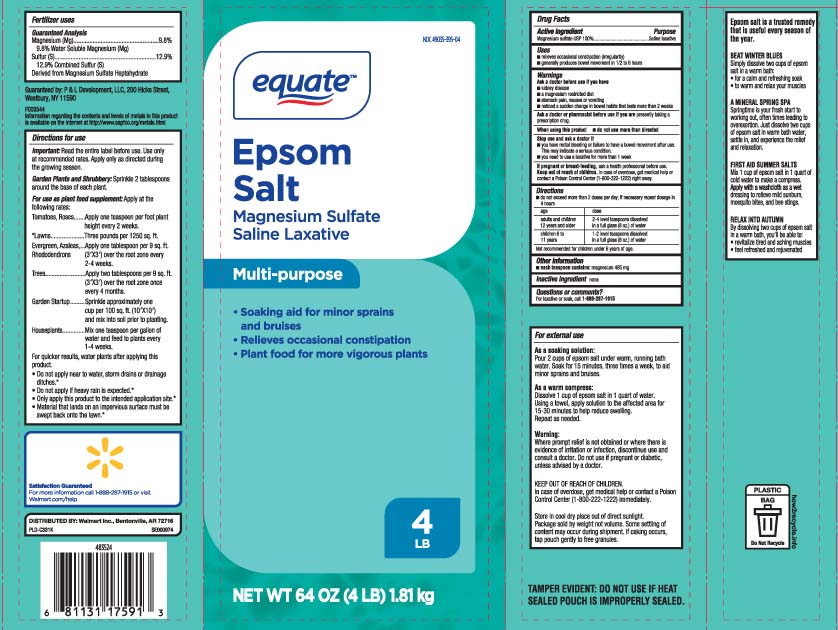 DRUG LABEL: Epsom Salt
NDC: 49035-395 | Form: GRANULE
Manufacturer: EQUATE (Wal-Mart Stores, Inc.) (see also WAL-MART INC)
Category: otc | Type: HUMAN OTC DRUG LABEL
Date: 20260209

ACTIVE INGREDIENTS: MAGNESIUM SULFATE, UNSPECIFIED 1 g/1 g

Drug Facts

Active ingredient

Magnesium sulfate USP 100%

Purpose

Saline laxative

Uses

- relieves occasional constipation (irregularity)
- generally produces bowel movement in 1/2 to 6 hours

Warnings

Ask a doctor before use if you have

- kidney disease
- a magnesium restricted diet
- stomach pain, nausea or vomiting
- noticed a sudden change in bowel habits that lasts more than 2 weeks

Ask a doctor or pharmacist before use if you are

presently taking a prescription drug.

When using this product

- do not use more than directed

Stop use and ask a doctor if

- you have rectal bleeding or failure to have a bowel movement after use. This may indicate a serious condition.
- you need to use a laxative for more than 1 week

If pregnancy or breast-feeding,

ask a health professional before use.

Keep out of reach of children.

In case of overdose, get medical help or contact a Poison Control Center (1-800-222-1222) right away.

Directions

- do not exceed more than 2 doses per day; if necessary repeat dosage in 4 hours

age | dose
adults and children 12 years and older | 2-4 level teaspoons dissolved in a full glass (8oz) of water
children 6 to 11 years | 1-2 level teaspoons dissolved in a full glass (8oz) of water

Not recommended for children under 6 years of age.

Other information

- each teaspoon contains: magnesium 495 mg

Inactive ingredient

none

Questions or comments?

For laxative or soak, call 1-888-287-1915

Principal Display Panel

EPSOM SALTS

MAGNESIUM SULFATE, U.S.P.

Multi-purpose

- Soaking aid for minor sprains and bruise
- Relieves occasional constipation
- Plant food for bigger, more vigorous plants

Net Wt LB (kg)

TAMPER EVIDENT: DO NOT USE IF HEAT SEALED POUCH IS IMPROPERLY SEALED

DISTRIBUTED BY: Walmart Inc.,

Bentonville, AR 72716

Package Label

EQUATE Epsom Salt